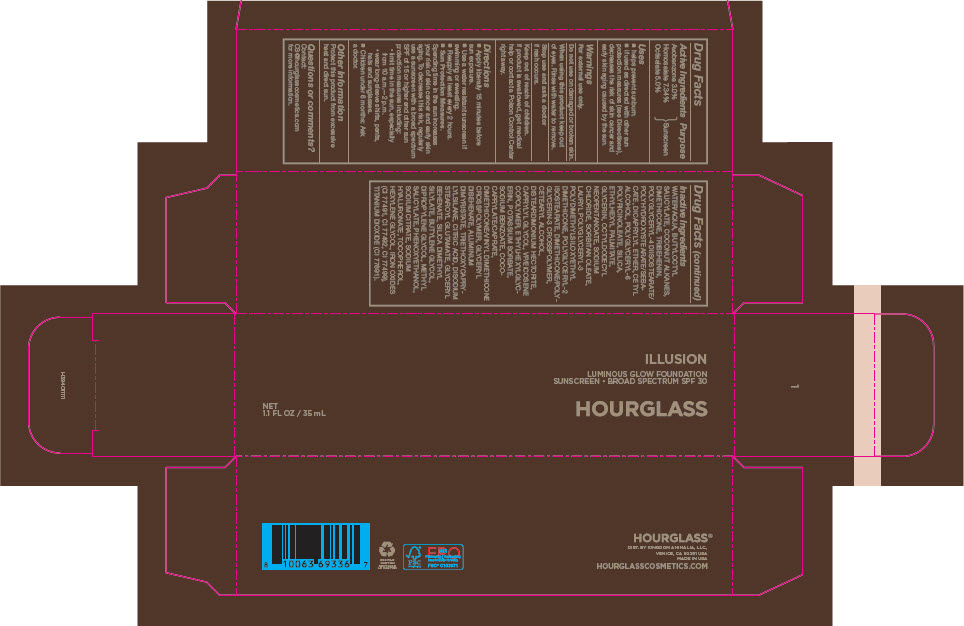 DRUG LABEL: ILLUSION LUMINOUS GLOW FOUNDATION
NDC: 42627-102 | Form: LOTION
Manufacturer: Kingdom Animalia, LLC DBA Hourglass Cosmetics
Category: otc | Type: HUMAN OTC DRUG LABEL
Date: 20250818

ACTIVE INGREDIENTS: AVOBENZONE 3 g/100 mL; HOMOSALATE 7.34 g/100 mL; OCTISALATE 5 g/100 mL
INACTIVE INGREDIENTS: WATER; BUTYLOCTYL SALICYLATE; COCONUT ALKANES; DIMETHICONE; POLYGLYCERYL-4 DIISOSTEARATE/POLYHYDROXYSTEARATE/SEBACATE; TRIBEHENIN; DICAPRYLYL ETHER; CETYL ALCOHOL; POLYGLYCERYL-6 POLYRICINOLEATE; SILICON DIOXIDE; ETHYLHEXYL PALMITATE; GLYCERIN; OCTYLDODECYL NEOPENTANOATE; SODIUM CHLORIDE; SORBITAN MONOOLEATE; Dimethicone/Polyglycerin-3 Crosspolymer; POLYGLYCERYL-2 ISOSTEARATE; CETOSTEARYL ALCOHOL; DISTEARDIMONIUM HECTORITE; CAPRYLYL GLYCOL; GLYCERYL BEHENATE/EICOSADIOATE; EICOSYL POVIDONE; ETHYLHEXYLGLYCERIN; COCOYL CAPRYLOCAPRATE; DIMETHICONE/VINYL DIMETHICONE CROSSPOLYMER (SOFT PARTICLE); ALUMINUM DIMYRISTATE; TRIETHOXYCAPRYLYLSILANE; CITRIC ACID MONOHYDRATE; DISODIUM STEAROYL GLUTAMATE; SILICA DIMETHYL SILYLATE; BUTYLENE GLYCOL; DIPROPYLENE GLYCOL; SODIUM CITRATE, UNSPECIFIED FORM; HYALURONATE SODIUM; TOCOPHEROL; HEXYLENE GLYCOL; POTASSIUM SORBATE; SODIUM BENZOATE; PHENOXYETHANOL; METHYL SALICYLATE; TITANIUM DIOXIDE; FERRIC OXIDE RED; FERRIC OXIDE YELLOW; FERROSOFERRIC OXIDE

ILLUSION LUMINOUS GLOW FOUNDATION

Drug Facts

Active Ingredients

Avobenzone 3.0%
Homosalate 7.34%
Octisalate 5.0%

Purpose

Sunscreen

Uses

- helps prevent sunburn.
- if used as directed with other sun protection measures (see Directions), decreases the risk of skin cancer and early skin aging caused by the sun.

Warnings

For external use only.

Do not use on damaged or broken skin.

When using this product keep out of eyes. Rinse with water to remove.

Stop use and ask a doctor if rash occurs.

Keep out of reach of children.

If product is swallowed, get medical help or contact a Poison Control Center right away.

Directions

- Apply liberally 15 minutes before sun exposure.
- Use a water resistant sunscreen if swimming or sweating.
- Reapply at least every 2 hours.
- Sun Protection Measures.
  Spending time in the sun increases your risk of skin cancer and early skin aging. To decrease this risk, regularly use a sunscreen with a broad spectrum SPF of 15 or higher and other sun protection measures including:
  - limit time in the sun, especially from 10 a.m.—2 p.m.
  - wear long-sleeve shirts, pants, hats and sunglasses.
- Children under 6 months: Ask a doctor.

Other Information

Protect this product from excessive heat and direct sun.

Questions or comments?

Contact: CS@hourglasscosmetics.com for more information.

Inactive Ingredients

WATER/AQUA, BUTYLOCTYL SALICYLATE, COCONUT ALKANES, DIMETHICONE, TRIBEHENIN, POLYGLYCERYL-4 DIISOSTEARATE/POLYHYDROXYSTEARATE/SEBACATE, DICAPRYLYL ETHER, CETYL ALCOHOL, POLYGLYCERYL-6 POLYRICINOLEATE, SILICA, ETHYLHEXYL PALMITATE, GLYCERIN, OCTYLDODECYL NEOPENTANOATE, SODIUM CHLORIDE, SORBITAN OLEATE, LAURYL POLYGLYCERYL-3 POLYDIMETHYLSILOXYETHYL DIMETHICONE, POLYGLYCERYL-2 ISOSTEARATE, DIMETHICONE/POLYGLYCERIN-3 CROSSPOLYMER, CETEARYL ALCOHOL, DISTEARDIMONIUM HECTORITE, CAPRYLYL GLYCOL, VP/EICOSENE COPOLYMER, ETHYLHEXYLGLYCERIN, POTASSIUM SORBATE, SODIUM BENZOATE, COCOCAPRYLATE/CAPRATE, DIMETHICONE/VINYL DIMETHICONE CROSSPOLYMER, GLYCERYL DIBEHENATE, ALUMINUM DIMYRISTATE, TRIETHOXYCAPRYLYLSILANE, CITRIC ACID, DISODIUM STEAROYL GLUTAMATE, GLYCERYL BEHENATE, SILICA DIMETHYL SILYLATE, BUTYLENE GLYCOL, DIPROPYLENE GLYCOL, METHYL SALICYLATE, PHENOXYETHANOL, SODIUM CITRATE, SODIUM HYALURONATE, TOCOPHEROL, HEXYLENE GLYCOL, IRON OXIDES (CI 77491, CI 77492, CI 77499), TITANIUM DIOXIDE (CI 77891).

DIST. BY KINGDOM ANIMALIA, LLC.,
VENICE, CA 90291 USA

PRINCIPAL DISPLAY PANEL - 35 mL Tube Carton

ILLUSION

LUMINOUS GLOW FOUNDATION
SUNSCREEN • BROAD SPECTRUM SPF 30

HOURGLASS

NET
1.1 FL OZ / 35 mL